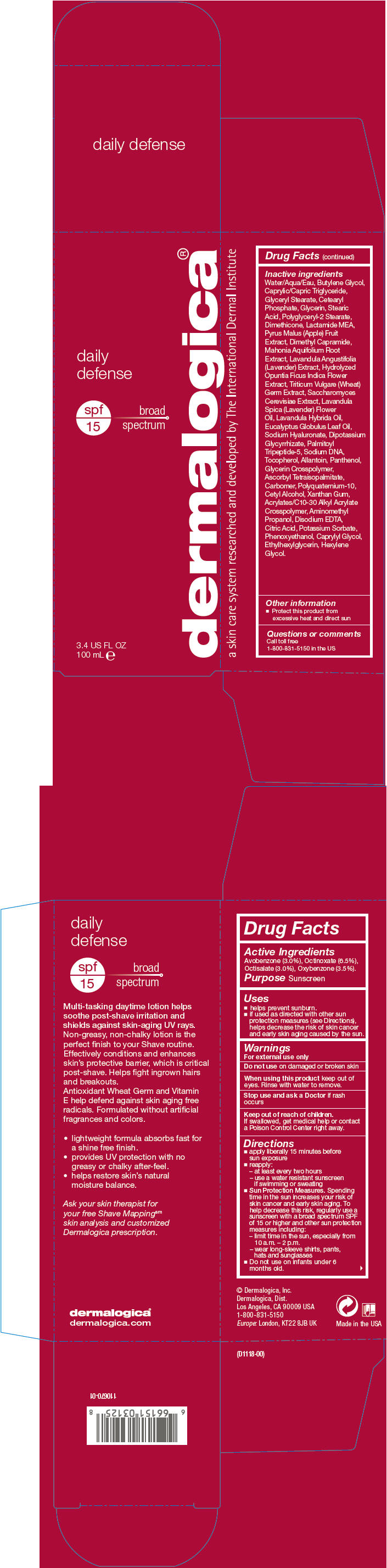 DRUG LABEL: Daily Defense 
NDC: 68479-800 | Form: LOTION
Manufacturer: Dermalogica, Inc.
Category: otc | Type: HUMAN OTC DRUG LABEL
Date: 20151118

ACTIVE INGREDIENTS: Avobenzone 30 mg/1 mL; Octinoxate 65 mg/1 mL; Octisalate 30 mg/1 mL; Oxybenzone 35 mg/1 mL
INACTIVE INGREDIENTS: Water; Butylene Glycol; Medium-Chain Triglycerides; Glyceryl Monostearate; Cetyl Phosphate; Glycerin; Stearic Acid; Dimethicone; N-Lactoyl Ethanolamine; Apple; Dimethyl Capramide; Mahonia Aquifolium Root; Lavandula Angustifolia Flowering Top; Vitis Vinifera Seed; Wheat Germ; Saccharomyces Cerevisiae; Hyaluronate Sodium; Phenoxyethanol; Cetyl Alcohol; Panthenol; Lavender Oil; Lavandin Oil; Eucalyptus Oil; Ascorbyl Tetraisopalmitate; Tocopherol; Allantoin; Palmitoyl Tripeptide-5; Carbomer Homopolymer Type C (Allyl Pentaerythritol Crosslinked); Sodium NA-22; Edetate Disodium; Ethylhexylglycerin; Glycyrrhizinate Dipotassium; Polidronium Chloride; Egg Phospholipids; Aminomethylpropanol; Citric Acid Monohydrate; Xanthan Gum; Carbomer Interpolymer Type A (Allyl Sucrose Crosslinked); Caprylyl Glycol; Hexylene Glycol; Potassium Sorbate

Daily Defense
SPF 15

Drug Facts

Active Ingredients

Avobenzone (3.0%), Octinoxate (6.5%), Octisalate (3.0%), Oxybenzone (3.5%).

Purpose

Sunscreen

Uses

- helps prevent sunburn.
- if used as directed with other sun protection measures (see Directions), helps decrease the risk of skin cancer and early skin aging caused by the sun.

Warnings

For external use only

Do not use on damaged or broken skin

When using this product keep out of eyes. Rinse with water to remove.

Stop use and ask a Doctor if rash occurs

Keep out of reach of children.

If swallowed, get medical help or contact a Poison Control Center right away.

Directions

- apply liberally 15 minutes before sun exposure
- reapply:
  1. at least every two hours
  2. use a water resistant sunscreen if swimming or sweating
- Sun Protection Measures. Spending time in the sun increases your risk of skin cancer and early skin aging. To help decrease this risk, regularly use a sunscreen with a broad spectrum SPF of 15 or higher and other sun protection measures including:
  1. limit time in the sun, especially from 10 a.m. – 2 p.m.
  2. wear long-sleeve shirts, pants, hats and sunglasses
- Do not use on infants under 6 months old.

Inactive ingredients

Water/Aqua/Eau, Butylene Glycol, Caprylic/Capric Triglyceride, Glyceryl Stearate, Cetearyl Phosphate, Glycerin, Stearic Acid, Polyglyceryl-2 Stearate, Dimethicone, Lactamide MEA, Pyrus Malus (Apple) Fruit Extract, Dimethyl Capramide, Mahonia Aquifolium Root Extract, Lavandula Angustifolia (Lavender) Extract, Hydrolyzed Opuntia Ficus Indica Flower Extract, Triticum Vulgare (Wheat) Germ Extract, Saccharomyces Cerevisiae Extract, Lavandula Spica (Lavender) Flower Oil, Lavandula Hybrida Oil, Eucalyptus Globulus Leaf Oil, Sodium Hyaluronate, Dipotassium Glycyrrhizate, Palmitoyl Tripeptide-5, Sodium DNA, Tocopherol, Allantoin, Panthenol, Glycerin Crosspolymer, Ascorbyl Tetraisopalmitate, Carbomer, Polyquaternium-10, Cetyl Alcohol, Xanthan Gum, Acrylates/C10-30 Alkyl Acrylate Crosspolymer, Aminomethyl Propanol, Disodium EDTA, Citric Acid, Potassium Sorbate, Phenoxyethanol, Caprylyl Glycol, Ethylhexylglycerin, Hexylene Glycol.

Other information

- Protect this product from excessive heat and direct sun

Questions or comments

Call toll free 1-800-831-5150 in the US

PRINCIPAL DISPLAY PANEL - 100 mL Tube Carton

daily
defense

spf
15
broad
spectrum

dermalogica®

3.4 US FL OZ
100 mL e